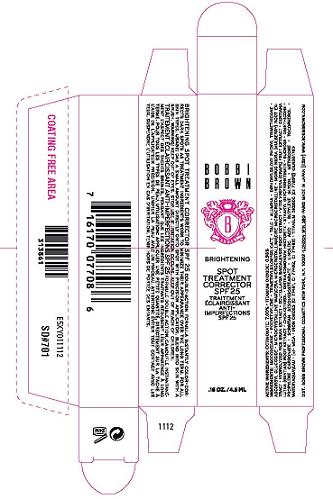 DRUG LABEL: BRIGHTENING SPOT TREATMENT CORRECTOR
NDC: 64141-003 | Form: CREAM
Manufacturer: Bobbi Brown Professional Cosmetics Inc
Category: otc | Type: HUMAN OTC DRUG LABEL
Date: 20100419

ACTIVE INGREDIENTS: OCTINOXATE 7 mL/100 mL; TITANIUM DIOXIDE 0.98 mL/100 mL

ACTIVE INGREDIENT

ACTIVE INGREDIENTS: OCTINOXATE 7.0% [] TITANIUM DIOXIDE 0.98%

WHEN USING

USAGE: DAB A SMALL AMOUNT DIRECTLY ONTO SPOT WITH PRECISION APPLICATOR. BLEND INTO SKIN WITH A BRUSH.

WARNINGS

WARNING: KEEP OUT OF EYES. STOP USE IF IRRITATION OCCURS. KEEP OUT OF REACH OF CHILDREN.

PACKAGE LABEL

PRINCIPAL DISPLAY PANEL:
BOBBI BROWN
BRIGHTENING
SPOT
TREATMENT
CORRECTOR
SPF 25
0.16 OZ/ 4.5 ML
BOBBI BROWN PROFESSIONAL COSMETICS INC
600 MADISON AVE
NEW YORK, NY 10022